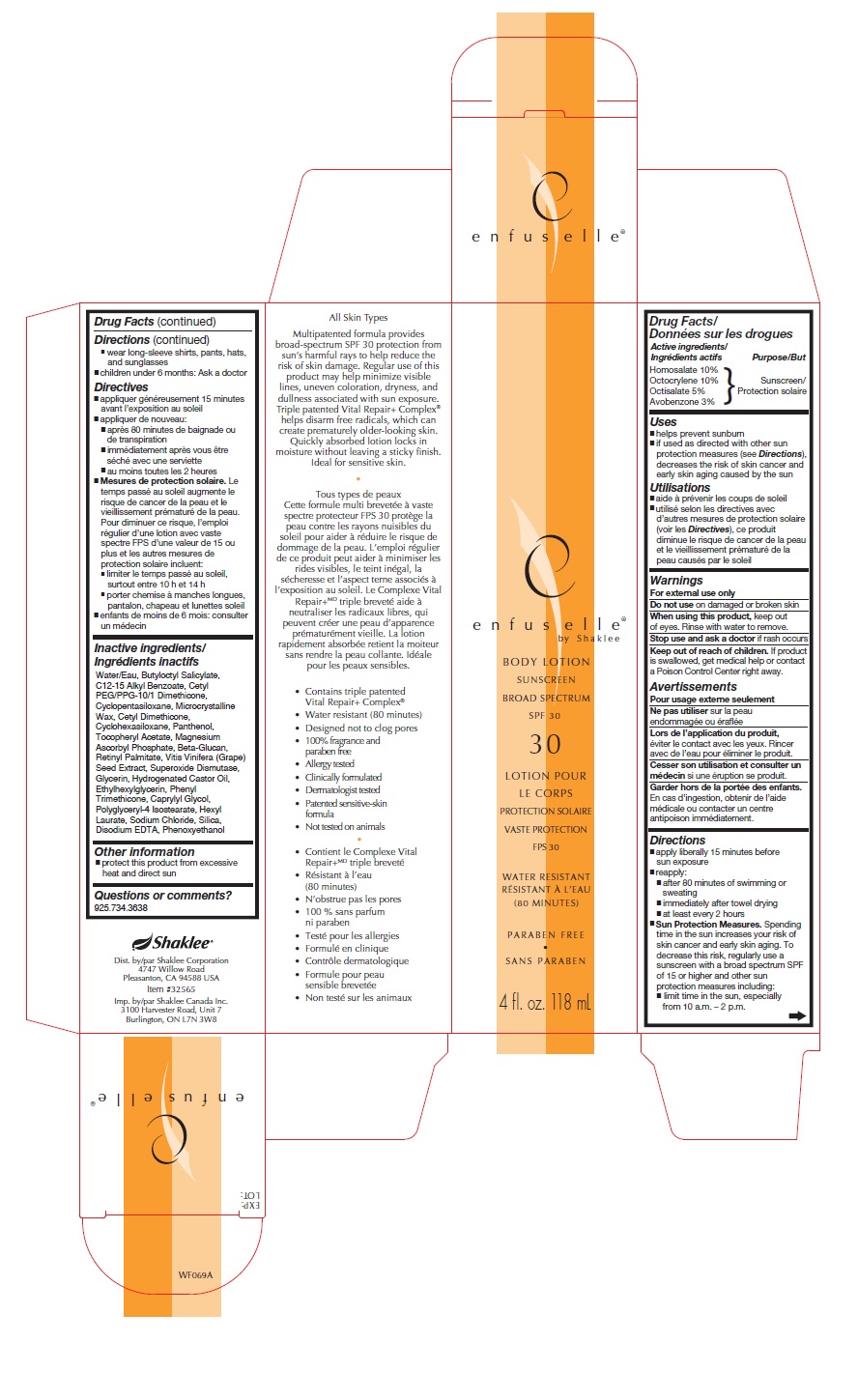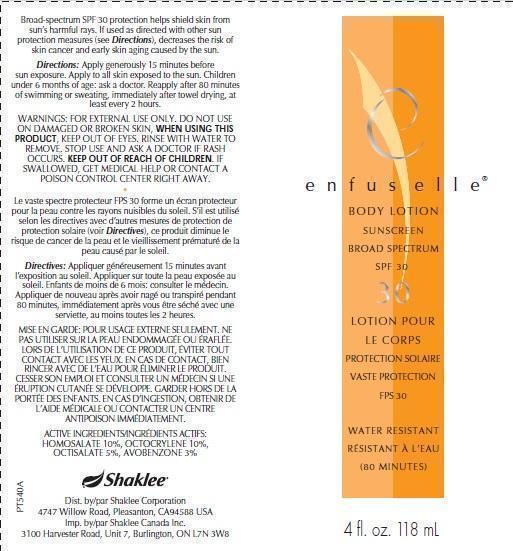 DRUG LABEL: enfuselle BODY SUNSCREEN BROAD SPECTRUM SPF 30
NDC: 59899-007 | Form: LOTION
Manufacturer: Shaklee Corporation
Category: otc | Type: HUMAN OTC DRUG LABEL
Date: 20231103

ACTIVE INGREDIENTS: OCTISALATE 50 mg/1 mL; AVOBENZONE 30 mg/1 mL; OCTOCRYLENE 100 mg/1 mL; HOMOSALATE 100 mg/1 mL
INACTIVE INGREDIENTS: BUTYLOCTYL SALICYLATE; ALKYL (C12-15) BENZOATE; CYCLOMETHICONE 5; MICROCRYSTALLINE WAX; CYCLOMETHICONE 6; PANTHENOL; .ALPHA.-TOCOPHEROL ACETATE; MAGNESIUM ASCORBYL PHOSPHATE; VITAMIN A PALMITATE; VITIS VINIFERA SEED; GLYCERIN; HYDROGENATED CASTOR OIL; ETHYLHEXYLGLYCERIN; PHENYL TRIMETHICONE; CAPRYLYL GLYCOL; POLYGLYCERYL-4 ISOSTEARATE; HEXYL LAURATE; SODIUM CHLORIDE; SILICON DIOXIDE; EDETATE DISODIUM; PHENOXYETHANOL; WATER

enfuselle BODY LOTION SUNSCREEN BROAD SPECTRUM SPF 30

Drug Facts:

Active ingredients

Homosalate 10% Octocrylene 10% Octisalate 5% Avobenzone 3%

Purpose

Sunscreen

Uses

- helps prevent sunburn
- if used as directed with other sun protection measures (see decreases the risk of skin cancer and early skin aging caused by the sun), Directions

Warnings

For external use only

on damaged or broken skin Do not use

WHEN USING

keep out of eyes. Rinse with water to remove When using this product

STOP USE

if rash occurs Stop use and ask a doctor

KEEP OUT OF REACH OF CHILDREN

If product is swallowed, get medical help or contact a Poison Control Center right away. Keep out of reach of children.

Directions

- apply liberally 15 minutes before sun exposure.
- reapply:
  - after 80 minutes of swimming or sweating
  - immediately after towel drying
  - at least every 2 hours.
- Spending time in the sun increases your risk of skin cancer and early skin aging. To decrease the risk, regularly use a sunscreen with a broad spectrum SPF value of 15 or higher and other sun protection measures including: Sun Protection Measures.
  - limit time in the sun, especially from 10 a.m. - 2 p.m.
  - wear long-sleeved shirts, pants, hats, and sunglasses.
- children under 6 months: Ask a doctor

Inactive ingredients:

Water/Eau, Butyloctyl Salicylate, C12-15 Alkyl Benzoate, Cetyl PEG/PPG-10/1 Dimethicone, Cyclopentasiloxane, Microcrystalline Wax, Cetyl Dimethicone, Cyclohexasiloxane, Panthenol, Tocopheryl Acetate, Magnesium Ascorbyl Phosphate, Beta-Glucan, Retinyl Palmitate, Vitis Vinifera (Grape) Seed Extract, Superoxide Dismutase, Glycerin, Hydrogenated Castor Oil, Ethylhexylglycerin, Phenyl Trimethicone, Caprylyl Glycol, Polyglyceryl-4 Isostearate, Hexyl Laurate, Sodium Chloride, Silica, Disodium EDTA, Phenoxyethanol

Other Information

- protect this product from excessive heat and direct sun

Questions or comments?

925.734.3638

PRINCIPAL DISPLAY PANEL CARTON

WATER RESISTANT

PARABEN FREE

4 fl. oz. 118 mL

All Skin Types Multipatented formula provides broad-spectrum SPF 30 protection from sun’s harmful rays to help reduce the risk of skin damage. Regular use of this product may help minimize visible lines, uneven coloration, dryness, and dullness associated with sun exposure. Triple patented Vital Repair+ Complex® helps disarm free radicals, which can create prematurely older-looking skin. Quickly absorbed lotion locks in moisture without leaving a sticky finish. Ideal for sensitive skin.

• Contains triple patented Vital Repair+ Complex® • Water resistant (80 minutes) • Designed not to clog pores • 100% fragrance and paraben free • Allergy tested • Clinically formulated • Dermatologist tested • Patented sensitive-skin formula • Not tested on animals

Dist. by/par Shaklee Corporation 4747 Willow Road Pleasanton, CA 94588 USA Item #32565 Imp. by/par Shaklee Canada Inc. 3100 Harvester Road, Unit 7 Burlington, ON L7N 3W8

PRINCIPAL DISPLAY PANEL TUBE

Broad-spectrum SPF 30 protection helps shield skin from sun’s harmful rays. If used as directed with other sun protection measures (see Directions), decreases the risk of skin cancer and early skin aging caused by the sun.

Directions: Apply generously 15 minutes before sun exposure.